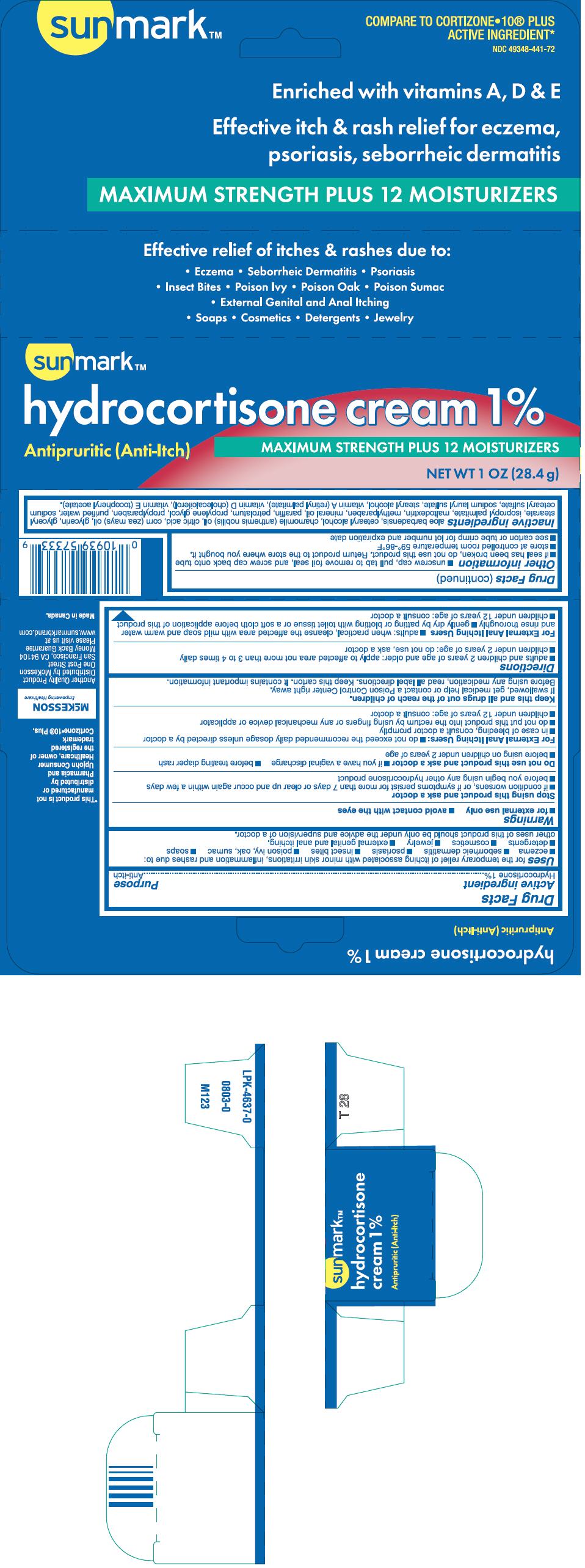 DRUG LABEL: SUNMARK HYDROCORTISONE PLUS
NDC: 49348-441 | Form: CREAM
Manufacturer: Strategic Sourcing Services LLC
Category: otc | Type: HUMAN OTC DRUG LABEL
Date: 20241004

ACTIVE INGREDIENTS: HYDROCORTISONE 1 g/100 g
INACTIVE INGREDIENTS: CETOSTEARYL ALCOHOL; CHAMOMILE FLOWER OIL; CITRIC ACID MONOHYDRATE; CORN OIL; GLYCERIN; GLYCERYL MONOSTEARATE; ISOPROPYL PALMITATE; MALTODEXTRIN; METHYLPARABEN; MINERAL OIL; PARAFFIN; PETROLATUM; PROPYLENE GLYCOL; PROPYLPARABEN; WATER; SODIUM CETOSTEARYL SULFATE; SODIUM LAURYL SULFATE; STEARYL ALCOHOL; VITAMIN A PALMITATE; CHOLECALCIFEROL; .ALPHA.-TOCOPHEROL ACETATE

sunmark™
Hydrocortisone Plus 12 Moisturizers

Drug Facts

Active ingredient

Hydrocortisone 1%

Purpose

Anti-itch

Uses

for the temporary relief of itching associated with minor skin irritations, inflammation and rashes due to:

- eczema
- seborrheic dermatitis
- psoriasis
- insect bites
- poison ivy, oak, sumac
- soaps
- detergents
- cosmetics
- jewelry
- external genital and anal itching.

other uses of this product should be only under the advice and supervision of a doctor.

Warnings

- for external use only
- avoid contact with the eyes

Stop using this product and ask a doctor

- if condition worsens, or if symptoms persist for more than 7 days or clear up and occur again within a few days
- before you begin using any other hydrocortisone product

Do not use this product and ask a doctor

- if you have a vaginal discharge
- before treating diaper rash
- before using on children under 2 years of age

For External Anal Itching Users

- do not exceed the recommended daily dosage unless directed by a doctor
- in case of bleeding, consult a doctor promptly
- do not put this product into the rectum by using fingers or any mechanical device or applicator
- children under 12 years of age: consult a doctor

Keep this and all drugs out of the reach of children.

If swallowed, get medical help or contact a Poison Control Center right away.

Before using any medication, read all label direction. Keep this carton. It contains important information.

Directions

- adults and children 2 years of age and older: apply to affected area not more than 3 to 4 times daily
- children under 2 years of age: do not use, ask a doctor

For External Anal Itching Users

- adults: when practical, cleanse the affected area with mild soap and warm water and rinse thoroughly
- gently dry by patting or blotting with toilet tissue or a soft cloth before application of this product
- children under 12 years of age: consult a doctor

Other information

- unscrew cap, pull tab to remove foil seal, and screw cap back onto tube
- if seal has been broken, do not use this product. Return product to the store where you bought it.
- store at controlled room temperature 59°-86°F
- see carton or tube crimp for lot number and expiration date

Inactive ingredients

aloe barbadensis, cetearyl alcohol, chamomile (anthemis nobilis) oil, citric acid, corn (zea mays) oil, glycerin, glyceryl stearate, isopropyl palmitate, maltodextrin, methylparaben, mineral oil, paraffin, petrolatum, propylene glycol, propylparaben, purified water, sodium cetearyl sulfate, sodium lauryl sulfate, stearyl alcohol, vitamin A (retinyl palmitate), vitamin D (cholecalciferol), vitamin E (tocopheryl acetate).

Distributed by McKesson
One Post Street
San Francisco, CA 94104

PRINCIPAL DISPLAY PANEL - 28.4 g Tube Carton

sunmark™

hydrocortisone cream 1%

Antipruritic (Anti-Itch)
MAXIMUM STRENGTH PLUS 12 MOISTURIZERS

NET WT 1 OZ (28.4 g)